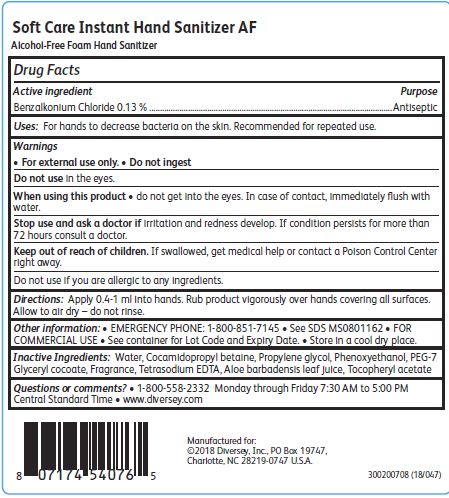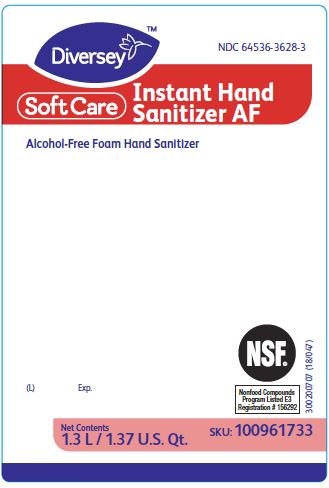 DRUG LABEL: Soft Care Instant Hand Sanitizer AF
NDC: 64536-3628 | Form: SOLUTION
Manufacturer: Diversey, Inc.
Category: otc | Type: HUMAN OTC DRUG LABEL
Date: 20241216

ACTIVE INGREDIENTS: BENZALKONIUM CHLORIDE 0.13 g/100 mL
INACTIVE INGREDIENTS: WATER; COCAMIDOPROPYL BETAINE; PROPYLENE GLYCOL; PHENOXYETHANOL; PEG-7 GLYCERYL COCOATE; EDETATE SODIUM; ALOE VERA LEAF; .ALPHA.-TOCOPHEROL ACETATE

Drug Facts

Active ingredient

Benzalkonium Chloride 0.13%

Purpose

Antiseptic

Uses:

For hands to decrease bacteria on the skin.

Recommended for repeated use.

Warnings

For external use only.

Do not ingest

Do not use in the eyes.

When using this product do not get into the eyes.

In case of contact, immediately flush with water.

Stop use and ask a doctor if irritation and redness develop.

If condition persists for more than 72 hours consult a doctor.

Keep out of reach of children.

If swallowed, get medical help or contact a Poison Control Center right away.

Do not use if you are allergic to any ingredients.

Directions:

Apply 0.4-1 ml into hands.

Rub product vigorously over hands covering all surfaces.

Allow to air dry - do not rinse.

Other information:

EMERGENCY PHONE: 1-800-851-7145

See SDS MS0881162

FOR COMMERCIAL USE

See container for Lot Code and Expiry Date.

Store in a cool dry place.

Inactive Ingredients:

Water, Cocamidopropyl betaine, Propylene glycol, Phenoxyethanol, PEG-7 Glyceryl cocoate, Fragrance, Tetrasodium EDTA, Aloe barbadensis leaf juice, Tocopheryl acetate

Questions or comments?

1-800-558-2332 Monday through Friday 7:30 AM to 5:00 PM Central Standard Time

www.sealedair.com

PACKAGE LABEL

NDC 64536-3628-3

Diversey

SoftCare

Instant Hand

Sanitizer AF

Alcohol-Free Foam Hand Sanitizer

(L) Exp.

NSF

Nonfood Compounds

Program Listed E3

Registration # 156292

Net Contents

1.3 L/ 1.37 U.S. Qt,

SKU: 100961733